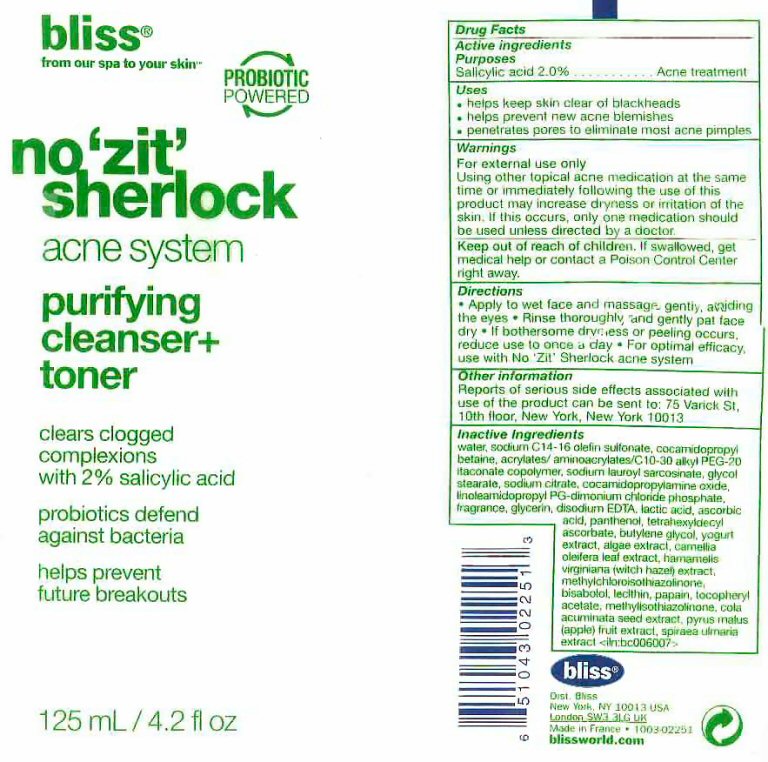 DRUG LABEL: no zit sherlock acne
NDC: 67038-108 | Form: GEL
Manufacturer: Bliss World LLC
Category: otc | Type: HUMAN OTC DRUG LABEL
Date: 20120608

ACTIVE INGREDIENTS: SALICYLIC ACID 2 mL/100 mL
INACTIVE INGREDIENTS: WATER; SODIUM C14 OLEFIN SULFONATE; COCAMIDOPROPYL BETAINE; SODIUM LAUROYL SARCOSINATE; GLYCOL STEARATE; SODIUM CITRATE; COCAMIDOPROPYLAMINE OXIDE; LINOLEAMIDOPROPYL PG-DIMONIUM CHLORIDE PHOSPHATE ; GLYCERIN; EDETATE DISODIUM; LACTIC ACID; ASCORBIC ACID; PANTHENOL; TETRAHEXYLDECYL ASCORBATE; BUTYLENE GLYCOL; CAMELLIA OLEIFERA LEAF; HAMAMELIS VIRGINIANA TOP; METHYLCHLOROISOTHIAZOLINONE; COLA ACUMINATA SEED; APPLE; FILIPENDULA ULMARIA WHOLE; LEVOMENOL; LECITHIN, SOYBEAN; PAPAIN; .ALPHA.-TOCOPHEROL ACETATE; METHYLISOTHIAZOLINONE

Active ingredients

Drug Facts

Active ingredients

Salicylic acid 2.0%

Purposes

Acne treatment

Keep out of reach of children. If swallowed, get medical help or contact a Poison Control Center right away.

Uses

- helps keep skin clear of blackheads
- helps prevent new acne blemishes
- penetrates pores to eliminate most acne pimples

Warnings

For external use only
Using other topical acne medication at the same time or immediately following the use of this product may increase dryness or irritation of the skin. If this occurs, only one medication should be used unless directed by a doctor.

Directions

- Apply to wet face and massage gently avoiding the eyes
- Rinse thoroughly and gently pat face dry
- if bothersome dryness and peeling occurs, reduce use to once a day
- For optimal efficacy, use with No 'Zit' Sherlock acne system

Other information

Reports on serious side effects associated with the use of the product can be sent to: 75 Varick St. 10th Floor, New York, New York 10013

Inactive Ingredients

water, sodium C14-16 olefin sulfonate, cocamidopropyl betaine, acrylates/Aminoacrylates/C-10-30 Alkyl PEG-20 Itaconate copolymer, sodium lauroyl sarcosinate, glycol stearate, sodium citrate, cocamidopropyl PG-dimonium chloride phosphate, fragrance, glycerin, disodium EDTA, lactic acid, ascorbic acid, panthenol, tetrahexyldecyl ascorbate, butylene glycol, yogurt extract, algae extract, camellia oleifera leaf extract, hamamelis virginiana (witch hazel) extract, methylchloroisothiazolinone, bisabolol, lecithin, papain, tocopheryl acetate, methylisothiazolinone, cola acuminata seed extract, pyrus malus (apple) fruit extract, spiraea ulmaria extract

Package Label

bliss from our spa to your skin PROBIOTIC POWERED
no 'zit' sherlock acne system purifying cleanser + toner

clears clogged complexions with 2% salicylic acid probiotics defend against bacteria helps prevent future breakouts

bliss dist Bliss New York NY 10013 USA London HA3 6DO UK 1003-02250 Made in France blissworld.com
125mL/4.2 fl oz